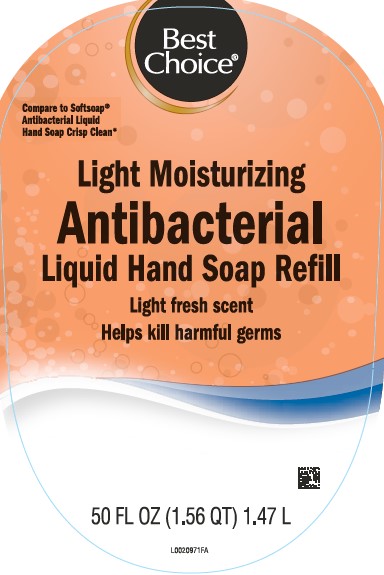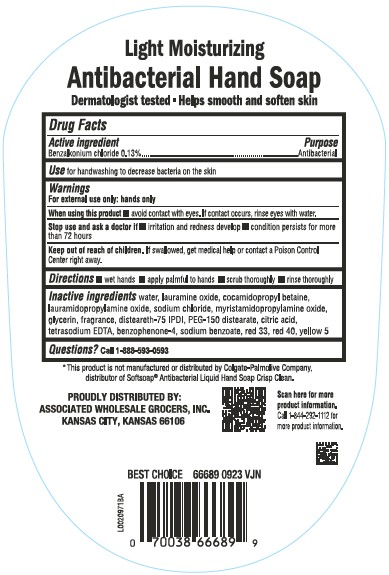 DRUG LABEL: Moisturizing Antibacterial
NDC: 63941-279 | Form: SOAP
Manufacturer: Valu Merchandisers Company
Category: otc | Type: HUMAN OTC DRUG LABEL
Date: 20260216

ACTIVE INGREDIENTS: BENZALKONIUM CHLORIDE 1.3 mg/1 mL
INACTIVE INGREDIENTS: WATER; LAURAMINE OXIDE; COCAMIDOPROPYL BETAINE; LAURAMIDOPROPYLAMINE OXIDE; SODIUM CHLORIDE; MYRISTAMIDOPROPYLAMINE OXIDE; GLYCERIN; DISTEARETH-75 ISOPHORONE DIISOCYANATE; PEG-150 DISTEARATE; CITRIC ACID MONOHYDRATE; EDETATE SODIUM; SULISOBENZONE; SODIUM BENZOATE; D&C RED NO. 33; FD&C RED NO. 40; FD&C YELLOW NO. 5

Best Choice 279.003/279AD-AE
Light Moisturizing Antibacterial Hand Soap

Claims

Light Moisturizing

Antibacterial Hand Soap

Dermatologist tested

Helps smooth and soften skin

Active ingredient

Benzalkonium chloride 0.13%

Purpose

Antibacterial

Use

for handwashing to decrease bacteria on the skin

Warnings

For external use only: hands only

When using this product

- avoid contact with eyes. If contact occurs, rinse eyes thoroughly with water.

Stop use and ask a doctor if

- irritation and redness develop
- condition persists for more than 72 hours

Keep out of reach of children.

If swallowed, get medical help or contact a Poison Control Center right away.

Directions

- wet hands
- apply palmful to hands
- scrub thoroughly
- rinse thoroughly

Inactive ingredients

water, lauramine oxide, cocamidopropyl betaine, lauramidopropylamine oxide, sodium chloride, myristamidopropylamine oxide, glycerin, fragrance, disteareth-75 IPDI, PEG-150 distearate, citric acid, tetrasodium EDTA, benzophenone-4, sodium benzoate, red 33, red 40, yellow 5

Questions?

Call 1-888-593-0593

Disclaimer

*This product is not manufactured or distributed by Colgate-Palmolive Company, distributor of Softsoap®Antibacterial Liquid Hand Soap Crisp Clean.

Adverse Reaction

PROUDLY DISTRIBUTED BY:

ASSOCIATED WHOLESALE GROCERS, INC.

KANSAS CITY, KS 66106

Scan here for more product information.

Call 1-844-292-1112 for more product information.

BEST CHOICE 66689 0923 VJN

Principal display panel

Best Choice®

Compare to Softsoap® Antibacterial Liquid Hand Soap Crisp Clean*

Light Moisturizing

Antibacterial

Liquid Hand Soap Refill

Light fresh scent

Helps kills harmful germs

50 FL OZ (1.56 QT) 1.47 L